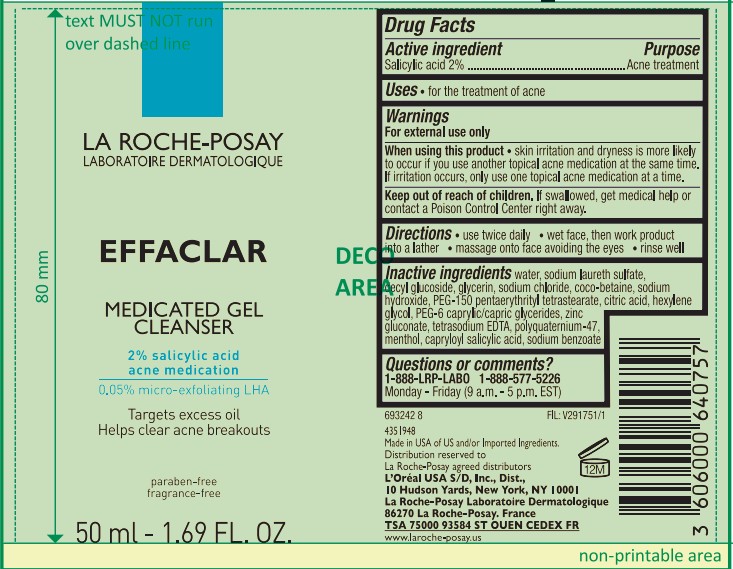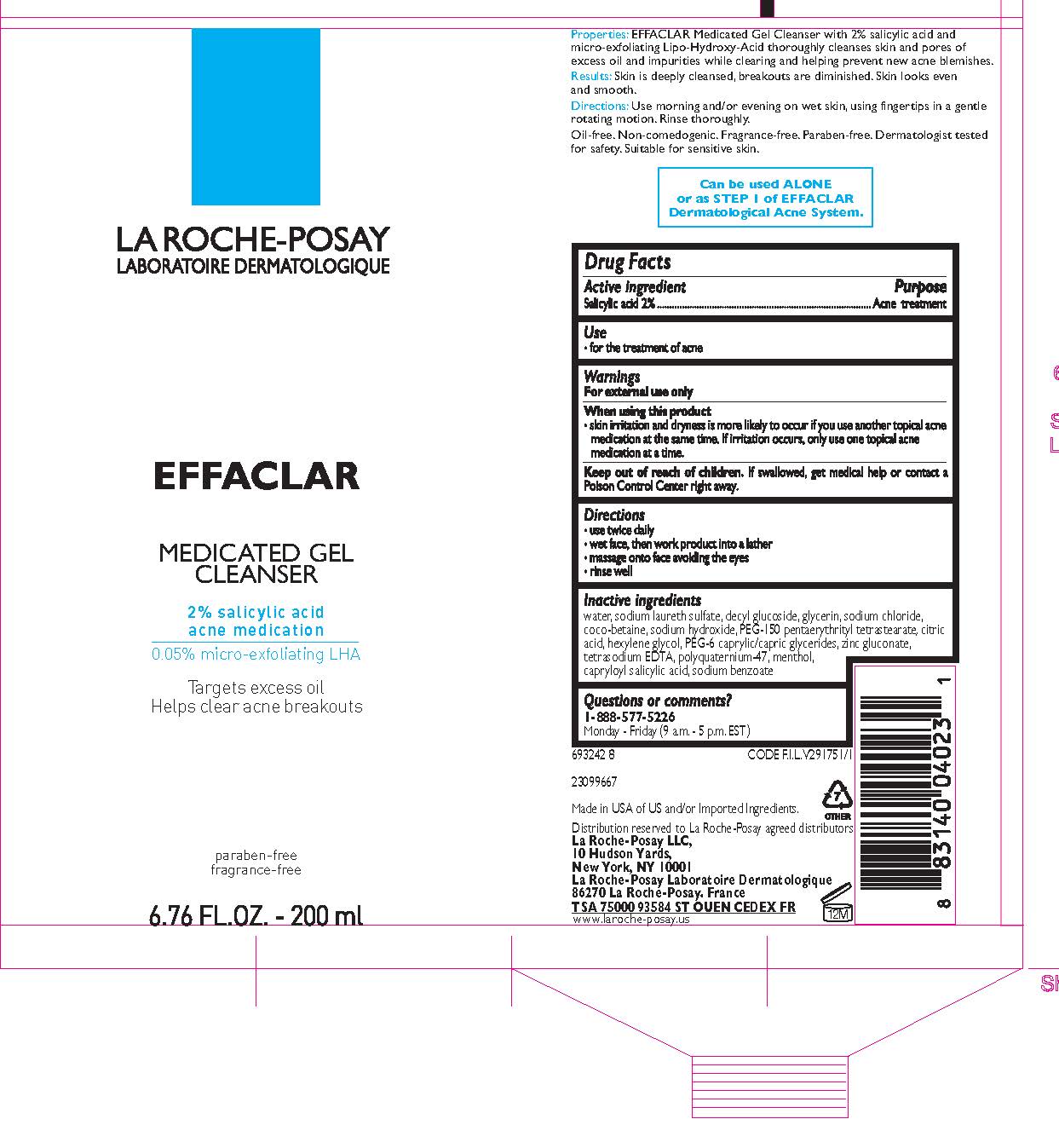 DRUG LABEL: La Roche Posay Effaclar Medicated Cleanser
NDC: 49967-402 | Form: GEL
Manufacturer: L'Oreal USA Products Inc
Category: otc | Type: HUMAN OTC DRUG LABEL
Date: 20250708

ACTIVE INGREDIENTS: SALICYLIC ACID 20 mg/1 mL
INACTIVE INGREDIENTS: WATER; SODIUM LAURETH SULFATE; DECYL GLUCOSIDE; GLYCERIN; SODIUM CHLORIDE; COCO-BETAINE; SODIUM HYDROXIDE; PEG-150 PENTAERYTHRITYL TETRASTEARATE; CITRIC ACID MONOHYDRATE; HEXYLENE GLYCOL; PEG-6 CAPRYLIC/CAPRIC GLYCERIDES; ZINC GLUCONATE; EDETATE SODIUM; POLYQUATERNIUM-47 (METHACRYLAMIDOPROPYLTRIMETHYLAMMONIUM CHLORIDE-CO-METHYL ACRYLATE-CO-ACRYLIC ACID 46:8:46; 1300000 MW); MENTHOL; CAPRYLOYL SALICYLIC ACID; SODIUM BENZOATE

Drug Facts

Active ingredient

Salicylic acid 2%

Purpose

Acne treatment

Use

for the treatment of acne

Warnings

For external use only

When using this product

skin irritation and dryness is more likely to occur if you use another topical acne medication at the same time. If irritation occurs, only use one topical acne medication at a time.

Keep out of reach of children.

If swallowed, get medical help or contact a Poison Control Center right away.

Directions

- use twice daily
- wet face, then work product into a lather
- massage onto face, avoiding the eyes
- rinse well

Inactive ingredients

water, sodium laureth sulfate, decyl glucoside, glycerin, sodium chloride, coco-betaine, sodium hydroxide, PEG-150 pentaerythrityl tetrastearate, citric acid, hexylene glycol, PEG-6 caprylic/capric glycerides, zinc gluconate, tetrasodium EDTA, polyquaternium-47, menthol, capryloyl salicylic acid, sodium benzoate

Questions or comments?

1-888-577-5226

Monday - Friday (9 a.m. - 5 p.m. EST)